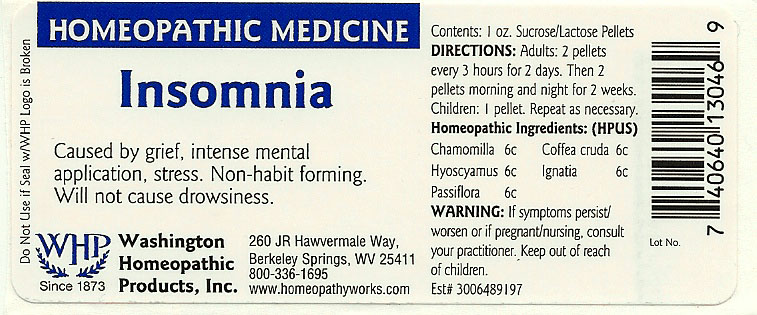 DRUG LABEL: Insomnia
NDC: 68428-021 | Form: PELLET
Manufacturer: Washington Homeopathic Products
Category: homeopathic | Type: HUMAN OTC DRUG LABEL
Date: 20191223

ACTIVE INGREDIENTS: MATRICARIA RECUTITA 6 [hp_C]/1 1; ARABICA COFFEE BEAN 6 [hp_C]/1 1; HYOSCYAMUS NIGER 6 [hp_C]/1 1; STRYCHNOS IGNATII SEED 6 [hp_C]/1 1; PASSIFLORA INCARNATA TOP 6 [hp_C]/1 1
INACTIVE INGREDIENTS: SUCROSE; LACTOSE

DRUG FACTS

ACTIVE INGREDIENTS

CHAMOMILLA 6C

COFFEA CRUDA 6C

HYOSCYAMUS 6C

IGNATIA 6C

PASSIFLORA 6C

USES

To relieve the symptoms of caused by grief, intense mental application, stress. Non-habit forming. Will not cause drowsiness.

KEEP OUT OF REACH OF CHILDREN

Keep this and all medicines out of reach of children.

INDICATIONS

CHAMOMILLA Irritability

COFFEA CRUDA Sleeplessness

HYOSCYAMUS Twitching

IGNATIA Sadness

PASSIFLORA Insomnia

STOP USE AND ASK DOCTOR

If symptoms persist/worsen or if pregnant/nursing, stop use and consult your practitioner.

DIRECTIONS

Adults 2 pellets every 3 hours for 2 days. Then 2 pellets morning and night for 2 weeks.

Children: 1 pellet. Repeat as necessary.

INACTIVE INGREDIENTS

Sucrose/Lactose

PRINCIPAL DISPLAY PANEL

Enter section text here